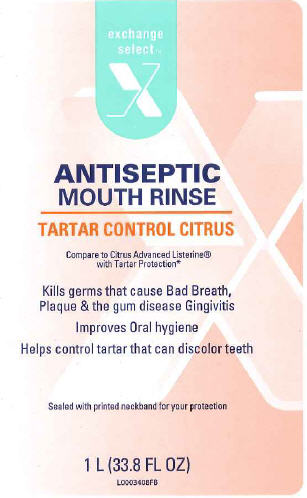 DRUG LABEL: Antiseptic
NDC: 55301-210 | Form: MOUTHWASH
Manufacturer: Exchange Select
Category: otc | Type: HUMAN OTC DRUG LABEL
Date: 20120326

ACTIVE INGREDIENTS: EUCALYPTOL .092 mL/100 L; MENTHOL .042 mL/100 L; METHYL SALICYLATE .060 mL/100 L; THYMOL .064 mL/100 L
INACTIVE INGREDIENTS: WATER; ALCOHOL; SORBITOL; POLYOXYL 40 HYDROGENATED CASTOR OIL; POLOXAMER 407; BENZOIC ACID; ZINC CHLORIDE; SUCRALOSE; SODIUM BENZOATE; FD&C YELLOW NO. 6; FD&C RED NO. 40

Drug Facts

Active ingredients
Eucalyptol 0.092% Menthol 0.024%
Methyl salicylate 0.060% thymol 0.064%

Purpose
Antigingivitis, Antiplaque

INDICATIONS AND USAGE

Use helps control plaque that leads to gingivitis

Warnings

Do not use if you have painful or swollen guns, pus from the gum line, loose teeth or increased spacing between
the teeth. see your dentist immediately. These may be signs of periodontitis, a serious form of gum disease.

Stop use and ask a dentist if gingivitis, bleeding, or redness persists for more than 2 weeks.

Keep out of reach of children. If more than used for rinsing is accidentally swallowed, get
medical help or contact a Poison Control Center right away.

Directions
adults and children 12 years of age and older - vigorously swish 20 mL (2/3 FL OZ or 4 teaspoonfuls) between teeth for 30 seconds then spit out; do not swallow
children under 12 years of age - consult a dentist or doctor
•this rinse is not intended to replace brushing or flossing

Other information cold weather may cloud this product. Its antiseptic propertied are not affected. Store at room temperature (59⁰-77⁰F).

INACTIVE INGREDIENT

Inactive ingredients water, alcohol (21.6%), sorbitol solution, flavoring, PEG-40 hydrogenated castor oil, poloxamer 407, benzoic acid, zinc chloride, sucralose and/or sodium saccharin, sodium benzoate, yellow 6, red 40

This product is not manufactured or distributed by Johnson + Johnson Healthcare Products, distributor of Listerine
DSP-TN-15000
DSP-MO-34
SDS-TN-15012

PACKAGE LABEL

Exchange
Select
ANTISEPTIC
MOUTH RINSE
TARTAR CONTROL CITRUS
Compare to Citrus Advanced Listerine with Tartar Protection
Kills germs that cause Bad Breath, Plaque + the gum disease Gingivitis
Improves Oral hygiene
Helps control tartar that can discolor teeth
Sealed with printed neckband for your protection
1 L (33.8 FL OZ)